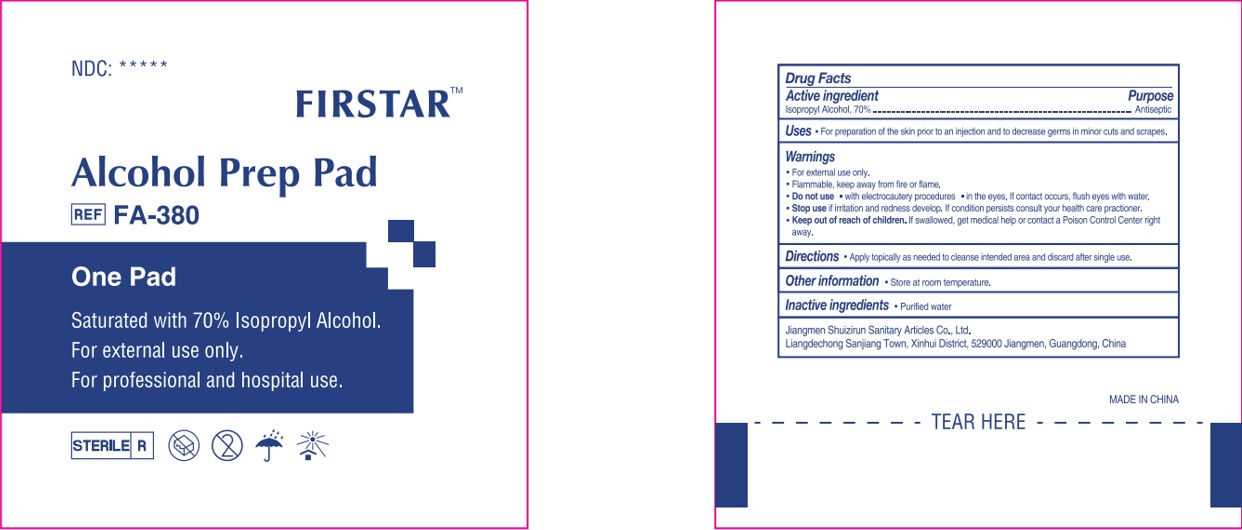 DRUG LABEL: FIRSTAR  Alcohol Prep Pad
NDC: 71734-112 | Form: CLOTH
Manufacturer: JIANGMEN SHUIZIRUN SANITARY ARTICLES CO., LTD.
Category: otc | Type: HUMAN OTC DRUG LABEL
Date: 20231115

ACTIVE INGREDIENTS: Isopropyl Alcohol 70 g/100 g
INACTIVE INGREDIENTS: water

DRUG FACTS

Active Ingredient

Isopropyl Alcohol ................ 70%

Purpose

Antiseptic

Uses:

For preparation of the skin prior to an injection and to decrease germs in minor cuts and scrapes.

Warnings

For external use only.

Flammable. Keep away from fire or flame.

- Do not use with electrocautery procedures; in the eyes. If contact accurs ,flush eyes with water.
- Stop use if irritation and redness develop. If condition persists consult your health care practioner.

Keep out of reach of children.

If swallowed, get medical help or contact a Poison Control Center right away.

Directions

Apply topically as needed to cleanse intended area and discard after single use.

Other Information: Store at room temperature.

Inactive Ingredients:

Purified Water